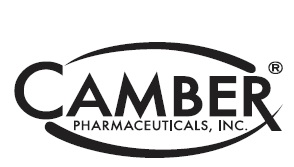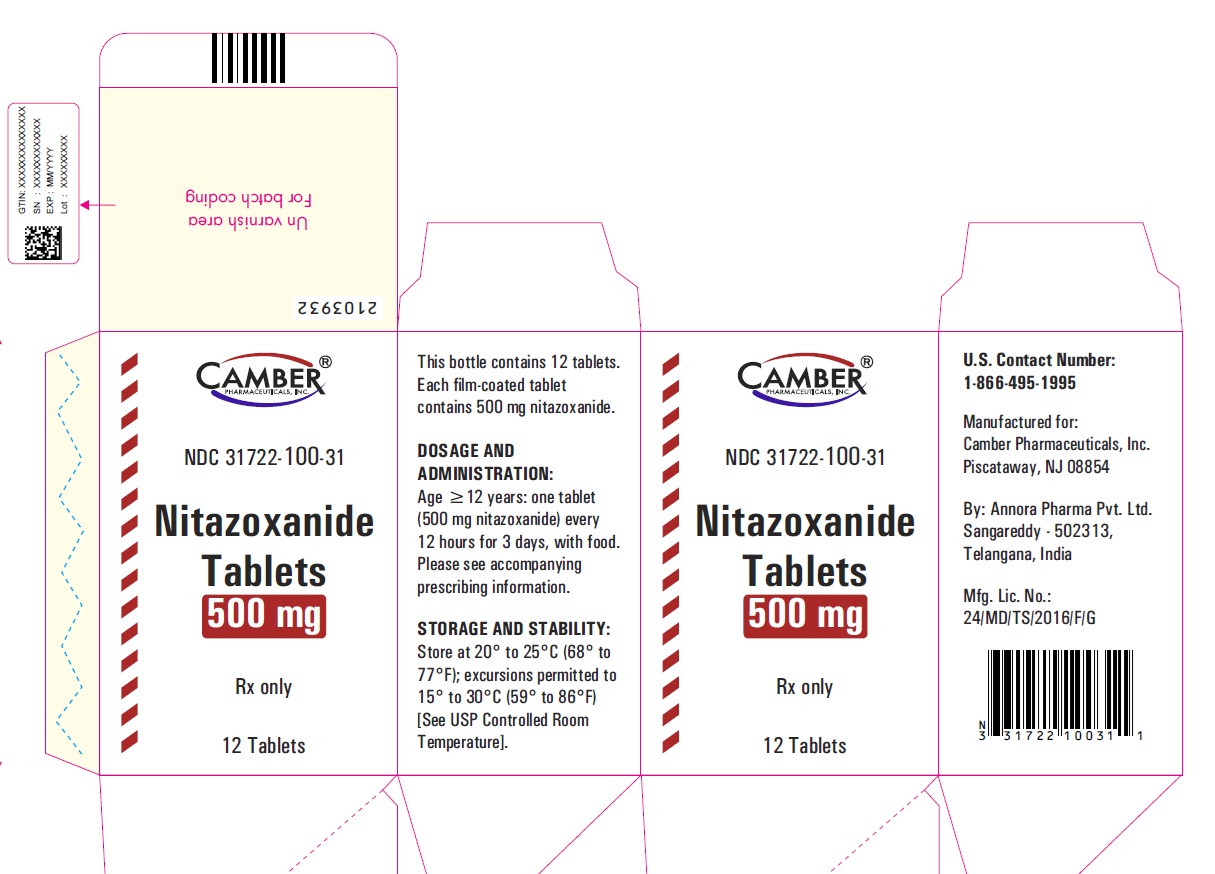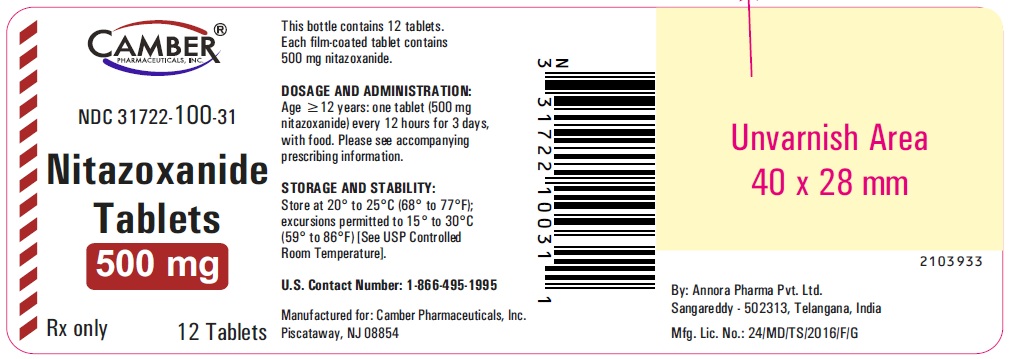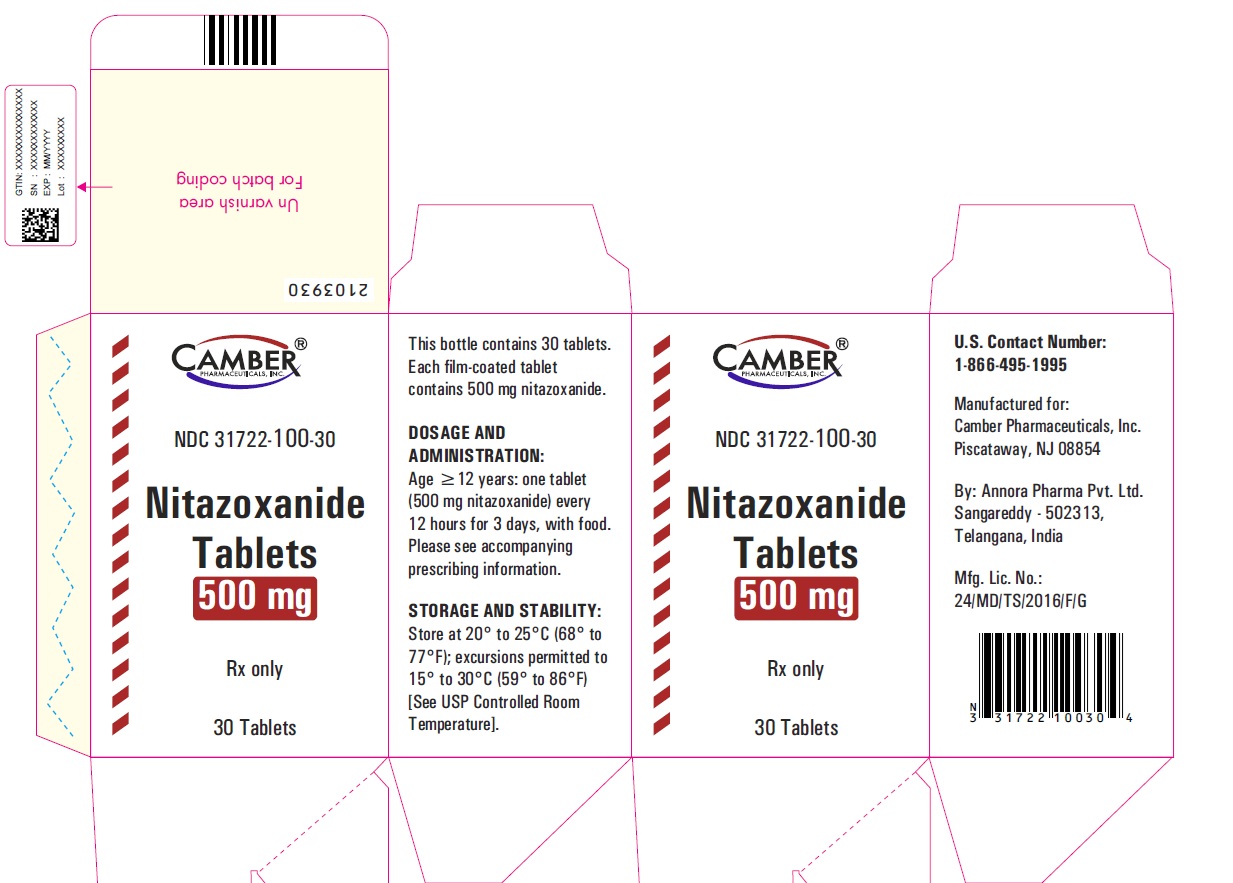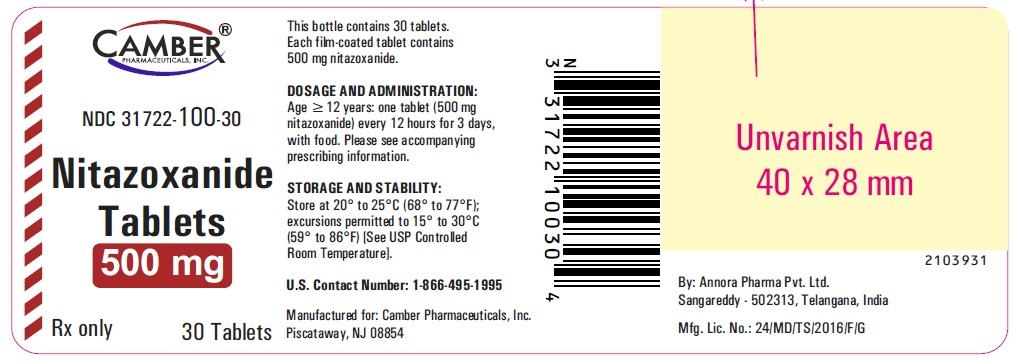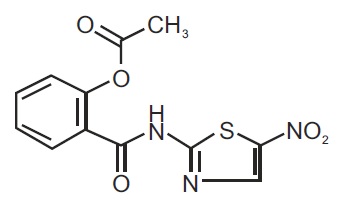 DRUG LABEL: Nitazoxanide

NDC: 31722-100 | Form: TABLET, FILM COATED
Manufacturer: Camber Pharmaceuticals, Inc.
Category: prescription | Type: HUMAN PRESCRIPTION DRUG LABEL
Date: 20251230

ACTIVE INGREDIENTS: NITAZOXANIDE 500 mg/1 1
INACTIVE INGREDIENTS: STARCH, CORN; D&C YELLOW NO. 10 ALUMINUM LAKE; FD&C BLUE NO. 2; FD&C YELLOW NO. 6; HYPROMELLOSE 2910 (15 MPA.S); SOYBEAN LECITHIN; MAGNESIUM STEARATE; POLYVINYL ALCOHOL, UNSPECIFIED; SODIUM STARCH GLYCOLATE TYPE A POTATO; TALC; TITANIUM DIOXIDE; XANTHAN GUM

HIGHLIGHTS OF PRESCRIBING INFORMATION

These highlights do not include all the information needed to use NITAZOXANIDE TABLETS safely and effectively. See full prescribing information for NITAZOXANIDE TABLETS.
NITAZOXANIDE tablets, for oral use
Initial U.S. Approval: 2002

1 INDICATIONS AND USAGE

Nitazoxanide tablets are antiprotozoal indicated for the treatment of diarrhea caused by Giardia lambliaor Cryptosporidium parvum (1).
Limitations of Use:
Nitazoxanide tablets have not been shown to be effective for the treatment of diarrhea caused by C. parvumin HIV-infected or immunodeficient patients (1).

2 DOSAGE AND ADMINISTRATION

• Nitazoxanide tablets should not be administered to pediatric patient 11 years of age or younger (2.1).
• Dosage for treatment of diarrhea caused by G.lambliaor C. parvum(2.1):

Age | Dosage | Duration
12 years and older | One 500 mg nitazoxanide tablet every 12 hours with food | 3 days

3 DOSAGE FORMS AND STRENGTHS

Nitazoxanide tablets: 500 mg (3).

4 CONTRAINDICATIONS

Hypersensitivity (4.1)

6 ADVERSE REACTIONS

The most common adverse reactions in ≥2% of patients were abdominal pain, headache, chromaturia, and nausea (6.1).
To report SUSPECTED ADVERSE REACTIONS, contact Annora Pharma Private Limited at 1-866-495-1995 or FDA at 1-800-FDA-1088 or www.fda.gov/medwatch.

7 DRUG INTERACTIONS

Competition for binding sites may occur when administered concurrently with other highly plasma protein-bound drugs with narrow therapeutic indices. Monitor for adverse reactions (7).

FULL PRESCRIBING INFORMATION

1 INDICATIONS AND USAGE

Diarrhea caused by Giardia lambliaor Cryptosporidium parvum:
Nitazoxanide tablets (patients 12 years and older) are indicated for the treatment of diarrhea caused by Giardia lambliaor Cryptosporidium parvum.
Limitations of Use
Nitazoxanide tablets have not been shown to be effective for the treatment of diarrhea caused by Cryptosporidium parvumin HIV-infected or immunodeficient patients [see Clinical Studies (14.2)] .

2 DOSAGE AND ADMINISTRATION

2.1 Recommended Dosage and Important Administration Instructions

Important Administration Instructions for Pediatric Patients 11 years of Age or Younger:
Nitazoxanide tablets should not be administered to pediatric patients 11 years of age or younger because a single tablet contains a greater amount of nitazoxanide than the recommended dosing in this pediatric age group.
Table 1. Recommended Dosage

Age | Dosage | Duration
12 years and older | One 500 mg nitazoxanide tablet taken orally every 12 hours with food | 3 days

3 DOSAGE FORMS AND STRENGTHS

3.1 Nitazoxanide Tablets (500 mg)

Green colored, round biconvex film-coated tablets debossed with “V1” on one side and “1” on the other side. Each tablet contains 500 mg of nitazoxanide.

4 CONTRAINDICATIONS

4.1 Hypersensitivity

Nitazoxanide tablets are contraindicated in patients with a prior hypersensitivity to nitazoxanide or any other ingredient in the formulations.

6 ADVERSE REACTIONS

6.1 Clinical Trials Experience

Because clinical trials are conducted under widely varying conditions, adverse reaction rates observed in the clinical trials of a drug cannot be directly compared to rates in the clinical trials of another drug and may not reflect the rates observed in practice.
The safety of nitazoxanide was evaluated in 2177 HIV-uninfected subjects 12 months of age and older who received nitazoxanide tablets or Alina for oral suspension at the recommended dose for at least three days. In pooled controlled clinical trials involving 536 HIV-uninfected subjects treated with nitazoxanide tablets or Alina for oral suspension, the most common adverse reactions were abdominal pain, headache, chromaturia and nausea (≥2%).
Safety data were analyzed separately for 280 HIV-uninfected subjects ≥12 years of age receiving nitazoxanide at the recommended dose for at least three days in 5 placebo-controlled clinical trials and for 256 HIV-uninfected subjects 1 through 11 years of age in 7 controlled clinical trials. There were no differences between the adverse reactions reported for nitazoxanide-treated subjects based upon age.

6.2 Postmarketing Experience

The following adverse reactions have been identified during post approval use of nitazoxanide. Because these reactions are reported voluntarily from a population of uncertain size, it is not always possible to reliably estimate their frequency or establish a causal relationship to drug exposure. The following is a list of adverse reactions spontaneously reported with nitazoxanide tablets which were not included in clinical trial listings:
Gastrointestinal disorders:diarrhea, gastroesophageal reflux disease
Nervous System disorders:dizziness
Respiratory, thoracic and mediastinal disorders:dyspnea
Skin and subcutaneous tissue disorders:rash, urticaria

7 DRUG INTERACTIONS

7.1 Highly Protein Bound Drugs with Narrow Therapeutic Indices

Tizoxanide (the active metabolite of nitazoxanide) is highly bound to plasma protein (>99.9%). Therefore, monitor for adverse reactions when administering nitazoxanide concurrently with other highly plasma protein-bound drugs with narrow therapeutic indices, as competition for binding sites may occur (e.g., warfarin).

8 USE IN SPECIFIC POPULATIONS

8.1 Pregnancy

Risk Summary
There are no data with nitazoxanide in pregnant women to inform a drug-associated risk. No teratogenicity or fetotoxicity was observed in animal reproduction studies with administration of nitazoxanide to pregnant rats and rabbits during organogenesis at exposures 30 and 2 times, respectively, the exposure at the maximum recommended human dose of 500 mg twice daily based on body surface area (BSA).
In the U.S. general population, the estimated background risk of major birth defects and miscarriage in clinically recognized pregnancies is 2% to 4% and 15% to 20%, respectively.
Data
Animal Data
Nitazoxanide was administered orally to pregnant rats at doses of 0, 200, 800 or 3200 mg/kg/day on gestation days 6 to 15. Nitazoxanide produced no evidence of systemic maternal toxicity when administered once daily via oral gavage to pregnant female rats at levels up to 3200 mg/kg/day during the period of organogenesis.
In rabbits, nitazoxanide was administered at doses of 0, 25, 50, or 100 mg/kg/day on gestation days 7 to 20. Oral treatment of pregnant rabbits with nitazoxanide during organogenesis resulted in minimal maternal toxicity and no external fetal anomalies.

8.2 Lactation

Risk Summary
No information regarding the presence of nitazoxanide in human milk, the effects on the breastfed infant, or the effects on milk production is available. The development and health benefits of breastfeeding should be considered along with the mother’s clinical need for nitazoxanide and any potential adverse effects on the breastfed infant from nitazoxanide or from the underlying maternal condition.

8.4 Pediatric Use

The safety and efficacy of nitazoxanide tablets for the treatment of diarrhea caused by G. lambliaor C. parvumin pediatric patients 12 to 17 years of age has been established based on three (3) randomized controlled studies with 47 pediatric subjects treated with nitazoxanide tablets 500 mg.
A single nitazoxanide tablet contains a greater amount of nitazoxanide than is recommended for use in pediatric patients 11 years or younger. [see Dosage and Administration (2.1)] .

8.5 Geriatric Use

Clinical studies of nitazoxanide tablets did not include sufficient numbers of subjects aged 65 and over to determine whether they respond differently from younger subjects. In general, the greater frequency of decreased hepatic, renal, or cardiac function, and of concomitant disease or other drug therapy in elderly patients should be considered when prescribing nitazoxanide tablets.

8.6 Renal and Hepatic Impairment

The pharmacokinetics of nitazoxanide in patients with compromised renal or hepatic function has not been studied.

8.7 HIV-Infected or Immunodeficient Patients

Nitazoxanide tablets have not been studied for the treatment of diarrhea caused by G. lambliain HIV-infected or immunodeficient patients. Nitazoxanide tablets have not been shown to be superior to placebo for the treatment of diarrhea caused by C. parvumin HIV-infected or immunodeficient patients [see Clinical Studies (14)] .

10 OVERDOSAGE

Limited information on nitazoxanide overdosage is available. In the event of overdose, gastric lavage may be appropriate soon after oral administration. Patients should be observed and given symptomatic and supportive treatment. There is no specific antidote for overdose with nitazoxanide. Because tizoxanide is highly protein bound (>99.9%), dialysis is unlikely to significantly reduce plasma concentrations of the drug.

11 DESCRIPTION

Nitazoxanide tablets contain the active ingredient, nitazoxanide, a synthetic antiprotozoal for oral administration. Nitazoxanide is off-white to yellow powder. It is practically insoluble in ethanol, water and soluble in N, N-dimethylacetamide. Chemically, nitazoxanide is 2-((5-Nitrothiazol-2-yl) carbamoyl) phenyl acetate. The molecular formula is C12H9N3O5S and the molecular weight is 307.28. The structural formula is:

Nitazoxanide tablets contain 500 mg of nitazoxanide and the following inactive ingredients: corn starch, D&C yellow #10 aluminum lake, FD&C blue #2, FD&C yellow #6, hypromellose, lecithin (soya), magnesium stearate, polyvinyl alcohol, pregelatinized starch, sodium starch glycolate, talc, titanium dioxide and xanthan gum.

12 CLINICAL PHARMACOLOGY

12.1 Mechanism of Action

Nitazoxanide is an antiprotozoal [see Microbiology (12.4)].

12.3 Pharmacokinetics

Absorption
Single Dosing:
Following oral administration of nitazoxanide tablets, the parent drug, nitazoxanide, is not detected in plasma. The pharmacokinetic parameters of the metabolites, tizoxanide and tizoxanide glucuronide are shown in Tables 2 and 3 below.
Table 2. Mean (± SD) plasma pharmacokinetic parameters of tizoxanide and tizoxanide glucuronide following administration of a single dose of one 500 mg nitazoxanide tablet with food to subjects ≥12 years of age

 | Tizoxanide |  |  | Tizoxanide Glucuronide
Age | Cmax(mcg/mL) | *Tmax (hr) | AUCτ (mcg•hr/mL) | Cmax (mcg/mL) | *Tmax (hr) | AUCτ (mcg•hr/mL)
12 to 7 years | 9.1 (6.1) | 4.0 (1 to 4) | 39.5 (24.2) | 7.3 (1.9) | 4.0 (2 to 8) | 46.5 (18.2)
≥18 years | 10.6 (2.0) | 3.0 (2 to 4) | 41.9 (6.0) | 10.5 (1.4) | 4.5 (4 to 6) | 63.0 (12.3)

*Tmaxis given as a Mean (Range)
Multiple dosing:
Following oral administration of a single nitazoxanide tablet every 12 hours for 7 consecutive days, there was no significant accumulation of nitazoxanide metabolites tizoxanide or tizoxanide glucuronide detected in plasma.
Bioavailability:
Alina for oral suspension is not bioequivalent to nitazoxanide tablets. The relative bioavailability of the suspension compared to the tablet was 70%.
When nitazoxanide tablets are administered with food, the AUCτof tizoxanide and tizoxanide glucuronide in plasma is increased almost two-fold and the Cmaxis increased by almost 50%.
Nitazoxanide tablets were administered with food in clinical trials and hence they are recommended to be administered with food [see Dosage and Administration (2.1)] .
Distribution
In plasma, more than 99% of tizoxanide is bound to proteins.
Elimination
Metabolism
Following oral administration in humans, nitazoxanide is rapidly hydrolyzed to an active metabolite, tizoxanide (desacetyl-nitazoxanide). Tizoxanide then undergoes conjugation, primarily by glucuronidation.
Excretion
Tizoxanide is excreted in the urine, bile and feces, and tizoxanide glucuronide is excreted in urine and bile. Approximately two-thirds of the oral dose of nitazoxanide is excreted in the feces and one-third in the urine.
Specific Populations
Pediatric Patients
The pharmacokinetics of tizoxanide and tizoxanide glucuronide following administration of nitazoxanide tablets in pediatric patients 12 to 17 years of age are provided above in Table 2. Mean (±SD) plasma pharmacokinetic parameters of tizoxanide and tizoxanide glcuronide following administration of a single dose of one 500 mg nitazoxanide tablet with food to subject ≥12 years of age.
Drug Interaction Studies
In vitrostudies demonstrated that tizoxanide has no significant inhibitory effect on cytochrome P450 enzymes.

12.4 Microbiology

Mechanism of Action
The antiprotozoal activity of nitazoxanide is believed to be due to interference with the pyruvate:ferredoxin oxidoreductase (PFOR) enzyme-dependent electron transfer reaction which is essential to anaerobic energy metabolism. Studies have shown that the PFOR enzyme from G. lambliadirectly reduces nitazoxanide by transfer of electrons in the absence of ferredoxin. The DNA-derived PFOR protein sequence of C. parvumappears to be similar to that of G. lamblia. Interference with the PFOR enzyme-dependent electron transfer reaction may not be the only pathway by which nitazoxanide exhibits antiprotozoal activity.
Resistance
A potential for development of resistance by C. parvumor G. lambliato nitazoxanide has not been examined.
Antimicrobial Activity
Nitazoxanide and its metabolite, tizoxanide, are active in vitroin inhibiting the growth of (i) sporozoites and oocysts of C. parvumand (ii) trophozoites of G. lamblia.
Susceptibility Test Methods
For protozoa such as C. parvumand G. lamblia, standardized tests for use in clinical microbiology laboratories are not available.

13 NONCLINICAL TOXICOLOGY

13.1 Carcinogenesis, Mutagenesis, Impairment of Fertility

Carcinogenesis
Long-term carcinogenicity studies have not been conducted.
Mutagenesis
Nitazoxanide was not genotoxic in the Chinese hamster ovary (CHO) cell chromosomal aberration assay or the mouse micronucleus assay. Nitazoxanide was genotoxic in one tester strain (TA 100) in the Ames bacterial mutation assay.
Impairment of Fertility
Nitazoxanide did not adversely affect male or female fertility in the rat at 2400 mg/kg/day (approximately 20 times the clinical adult dose adjusted for body surface area).

14 CLINICAL STUDIES

14.1 Diarrhea Caused by G. lamblia

Diarrhea caused by G. lambliain adults and adolescents 12 years of age or older:
In a double-blind, controlled trial (Study 1) conducted in Peru and Egypt in adults and adolescents with diarrhea and with one or more enteric symptoms (e.g., abdominal pain, nausea, vomiting, fever, abdominal distention, loss of appetite, flatulence) caused by G. lamblia, a three-day course of treatment with nitazoxanide tablets administered 500 mg twice daily was compared with a placebo tablet for 3 days. A second double-blind, controlled trial (Study 2) conducted in Egypt in adults and adolescents with diarrhea and with or without enteric symptoms (e.g., abdominal colic, abdominal tenderness, abdominal cramps, abdominal distention, fever, bloody stool) caused by G. lambliacompared nitazoxanide tablets administered 500 mg twice daily for 3 days to a placebo tablet. For both of these studies, clinical response was evaluated 4 to 7 days following the end of treatment. A clinical response of ‘well’ was defined as ‘no symptoms, no watery stools and no more than 2 soft stools with no hematochezia within the past 24 hours’ or ‘no symptoms and no unformed stools within the past 48 hours.’ The following clinical response rates were obtained:
Table 4. Adult and Adolescent Patients with Diarrhea Caused by G. lamblia Clinical Response Rates* 4 to 7 Days Post-therapy % (Number of Successes/Total)

 | Nitazoxanide Tablets | Placebo Tablets
Study 1 | 85% (46/54)¶ § | 44% (12/27)
Study 2 | 100% (8/8) | 30% (3/10)

*Includes all patients randomized with G. lambliaas the sole pathogen. Patients failing to complete the studies were treated as failures.
¶Clinical response rates statistically significantly higher when compared to placebo.
§The 95% confidence interval of the difference in response rates for the tablet and suspension is (-14%, 17%).
Some patients with ‘well’ clinical responses had G. lambliacysts in their stool samples 4 to 7 days following the end of treatment. The relevance of stool examination results in these patients is unknown. Patients should be managed based upon clinical response to treatment.

14.2 Diarrhea Caused by C. parvum

Diarrhea caused by C. parvumin adults and adolescents 12 years of age or older:
In a double-blind, controlled trial conducted in Egypt in adults and adolescents with diarrhea and with or without enteric symptoms (e.g., abdominal pain/cramps, nausea, vomiting) caused by C. parvum, a three-day course of treatment with nitazoxanide tablets administered 500 mg twice daily was compared with a placebo tablet for 3 days. Clinical response was evaluated 4 to 7 days following the end of treatment. A clinical response of ‘well’ was defined as ‘no symptoms, no watery stools and no more than 2 soft stools within the past 24 hours’ or ‘no symptoms and no unformed stools within the past 48 hours.’ The following clinical response rates were obtained:
Table 6. Clinical Response Rates in Adult and Adolescent Patients 4 to 7 Days Post-therapy % (Number of Successes/Total)

 | Nitazoxanide Tablets | Placebo Tablets
Intent-to-treat analysis* | 96% (27/28)¶ § | 41% (11/27)

*Includes all patients randomized with C. parvumas the sole pathogen. Patients failing to complete the study were treated as failures.
¶Clinical response rates statistically significantly higher when compared to placebo.
§The 95% confidence interval of the difference in response rates for the tablet and suspension is (-10%, 28%).
In a second double-blind, placebo-controlled trial of nitazoxanide tablets conducted in Egypt in adults and adolescents with diarrhea and with or without enteric symptoms (e.g., abdominal colic, abdominal cramps, epigastric pain) caused by C. parvumas the sole pathogen, clinical and parasitological response rates showed a similar trend to the first study. Clinical response rates, evaluated 2 to 6 days following the end of treatment, were 71% (15/21) in the nitazoxanide group and 42.9% (9/21) in the placebo group.
Some patients with ‘well’ clinical responses had C. parvumoocysts in their stool samples 4 to 7 days following the end of treatment. The relevance of stool examination results in these patients is unknown. Patients should be managed based upon clinical response to treatment.

16 HOW SUPPLIED/STORAGE AND HANDLING

16.1 Nitazoxanide Tablets (500 mg)

Nitazoxanide tablets 500 mg are green colored, round biconvex film-coated tablets debossed with “V1” on one side and “1” on the other side. Each tablet contains 500 mg of nitazoxanide. The tablets are packaged in HDPE bottles of 6, 12 and 30 tablets.
Bottles of 12 tablets NDC 31722-100-31
Bottles of 30 tablets NDC 31722-100-30
Bottles of 6 tablets NDC 31722-100-32
Store the tablets at 20° to 25°C (68° to 77°F); excursions permitted to 15° to 30°C (59° to 86°F). [See USP Controlled Room Temperature]

17 PATIENT COUNSELING INFORMATION

Advise patients and parents/caregivers of pediatric patients taking nitazoxanide tablets of the following information:
Dosage and Administration:
Nitazoxanide tablets should be taken with food.
Drug-drug Interactions:
Avoid concurrent warfarin use.

Manufactured for:

Camber Pharmaceuticals, Inc.
Piscataway, NJ 08854

By: Annora Pharma Pvt. Ltd.
Sangareddy - 502313, Telangana, India.

Revised: 05/2025

PACKAGE LABEL.PRINCIPAL DISPLAY PANEL

Nitazoxanide Tablets- 12's Container Label

Nitazoxanide Tablets- 12s Carton Label

Nitazoxanide Tablets- 30's Container Label

Nitazoxanide Tablets- 30's Carton Label